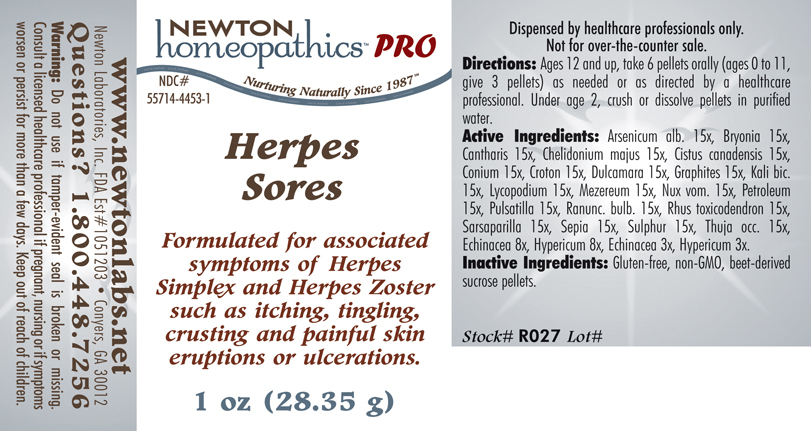 DRUG LABEL: Herpes Sores 
NDC: 55714-4453 | Form: PELLET
Manufacturer: Newton Laboratories, Inc.
Category: homeopathic | Type: HUMAN PRESCRIPTION DRUG LABEL
Date: 20110601

ACTIVE INGREDIENTS: Arsenic Trioxide 15 [hp_X]/1 g; Bryonia Alba Root 15 [hp_X]/1 g; Lytta Vesicatoria 15 [hp_X]/1 g; Chelidonium Majus 15 [hp_X]/1 g; Helianthemum Canadense 15 [hp_X]/1 g; Conium Maculatum Flowering Top 15 [hp_X]/1 g; Croton Tiglium Seed 15 [hp_X]/1 g; Solanum Dulcamara Top 15 [hp_X]/1 g; Graphite 15 [hp_X]/1 g; Potassium Dichromate 15 [hp_X]/1 g; Lycopodium Clavatum Spore 15 [hp_X]/1 g; Daphne Mezereum Bark 15 [hp_X]/1 g; Strychnos Nux-vomica Seed 15 [hp_X]/1 g; Kerosene 15 [hp_X]/1 g; Pulsatilla Vulgaris 15 [hp_X]/1 g; Ranunculus Bulbosus 15 [hp_X]/1 g; Toxicodendron Pubescens Leaf 15 [hp_X]/1 g; Smilax Regelii Root 15 [hp_X]/1 g; Sepia Officinalis Juice 15 [hp_X]/1 g; Sulfur 15 [hp_X]/1 g; Thuja Occidentalis Leafy Twig 15 [hp_X]/1 g; Echinacea, Unspecified 8 [hp_X]/1 g; Hypericum Perforatum 8 [hp_X]/1 g
INACTIVE INGREDIENTS: Sucrose

Herpes Sores

INDICATIONS & USAGE SECTION

HERPES SORES Formulated for associated symptoms of Herpes Simplex and Herpes Zoster such as itching, tingling, crusting and painful skin eruptions or ulcerations.

DOSAGE & ADMINISTRATION SECTION

Directions: Ages 12 and up, take 6 pellets orally (ages 0 to 11, give 3 pellets) as needed or as directed by a healthcare professional. Under age 2, crush or dissolve pellets in purified water.

ACTIVE INGREDIENT SECTION

Arsenicum alb. 15x, Bryonia 15x, Cantharis 15x, Chelidonium majus 15x, Cistus canadensis 15x, Conium 15x, Croton 15x, Dulcamara 15x, Graphites 15x, Kali bic. 15x, Lycopodium 15x, Mezereum 15x, Nux vom. 15x, Petroleum 15x, Pulsatilla 15x, Ranunc. bulb. 15x, Rhus toxicodendron 15x, Sarsaparilla 15x, Sepia 15x, Sulphur 15x, Thuja occ. 15x, Echinacea 8x, Hypericum 8x, Echinacea 3x, Hypericum 3x.

PURPOSE SECTION

Formulated for associated symptoms of Herpes Simplex and Herpes Zoster such as itching, tingling, crusting and painful skin eruptions or ulcerations.

INACTIVE INGREDIENT SECTION

Inactive Ingredients: Gluten-free, non-GMO, beet-derived sucrose pellets.

QUESTIONS? SECTION

www.newtonlabs.net Newton Laboratories, Inc. FDA Est # 1051203 - Conyers, GA 30012
Questions? 1.800.448.7256

WARNINGS SECTION

Warning: Do not use if tamper - evident seal is broken or missing. Consult a licensed healthcare professional if pregnant, nursing or if symptoms worsen or persist for more than a few days. Keep out of reach of children.

PREGNANCY OR BREAST FEEDING SECTION

Consult a licensed healthcare professional if pregnant or nursing or if symptoms worsen or persist for more than a few days.

KEEP OUT OF REACH OF CHILDREN SECTION

Keep out of reach of children.